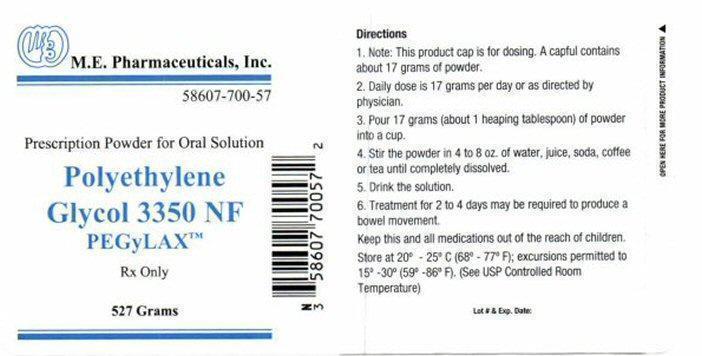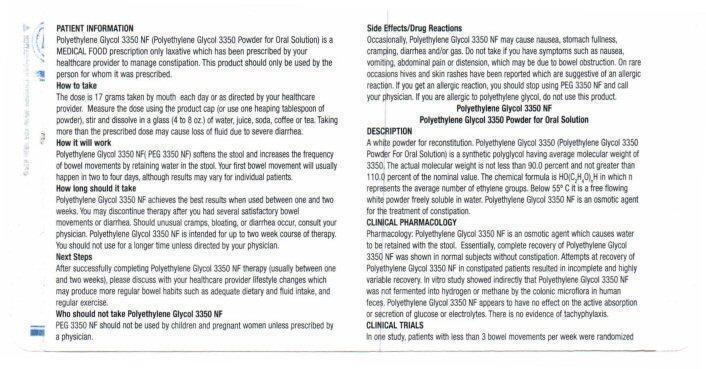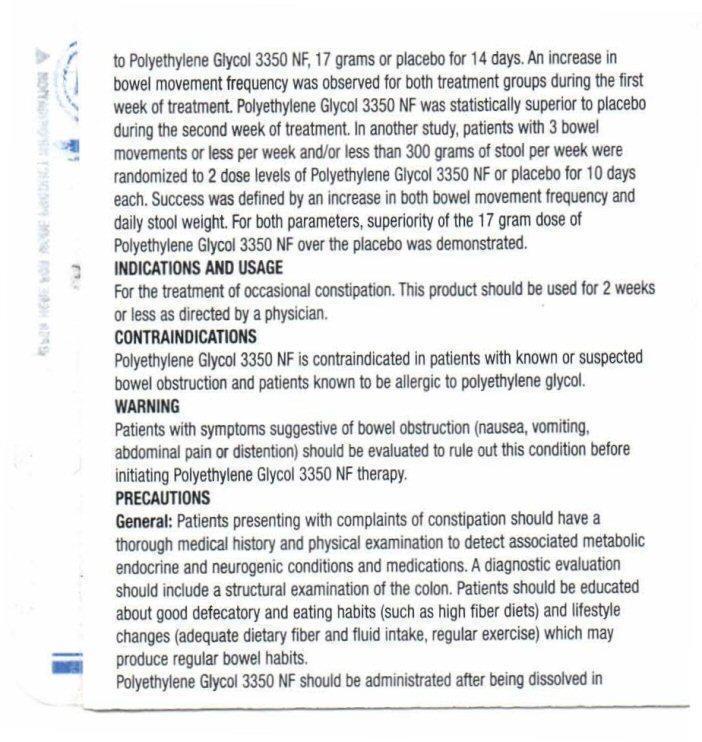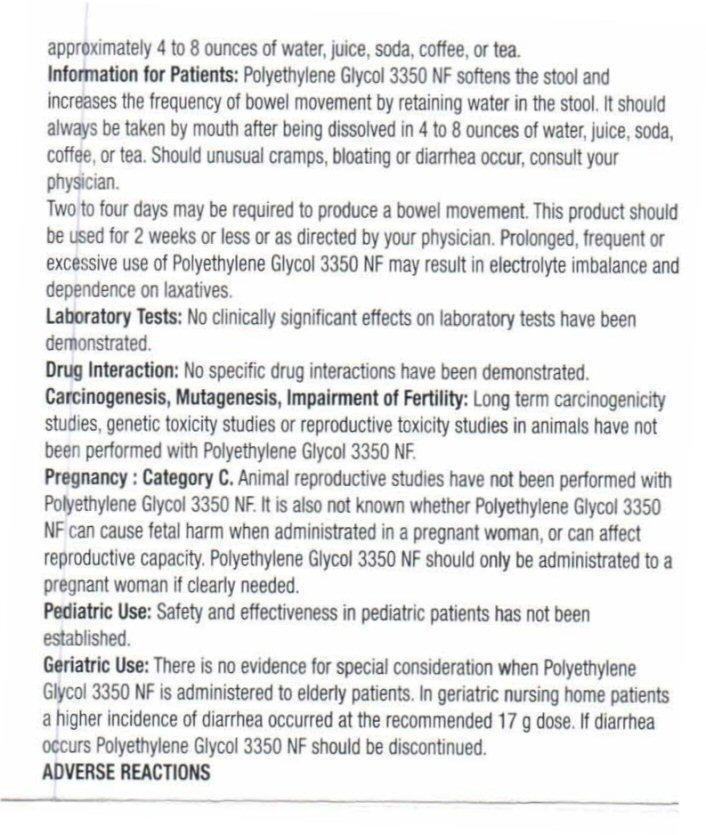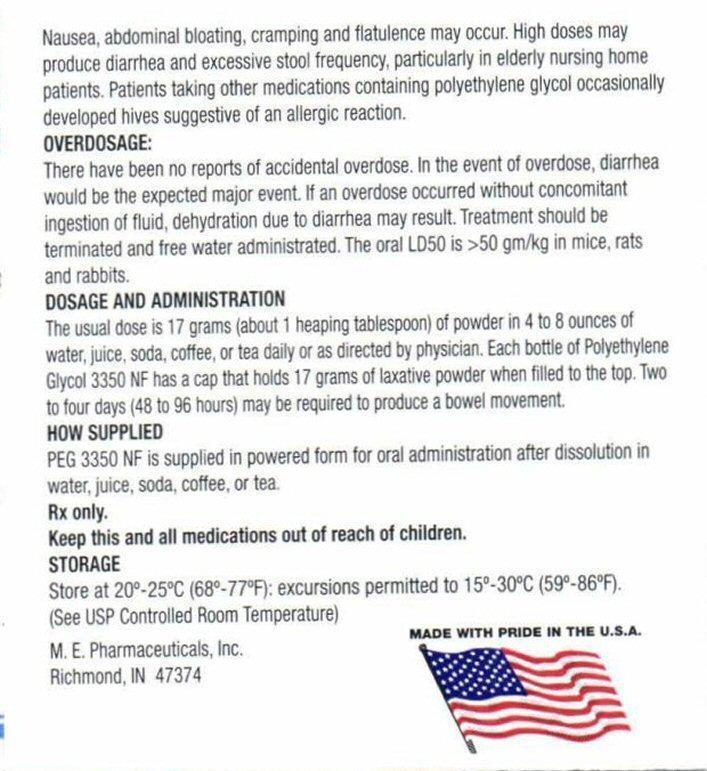 DRUG LABEL: Polyethylene Glycol 3350 NF
NDC: 58607-700 | Form: POWDER, FOR SOLUTION
Manufacturer: MARTIN EKWEALOR PHARMACEUTICALS, INC.
Category: prescription | Type: HUMAN PRESCRIPTION DRUG LABEL
Date: 20131213

ACTIVE INGREDIENTS: POLYETHYLENE GLYCOL 3350 17 g/17 g

Directions

1. Note: This product cap is for dosing. A capful contains about 17 grams of powder.
2. Daily dose is 17 grams per day or as directed by physician.
3. pour 17 grams (about 1 heaping tablespoon) of powder into a cup.
4. Stir the powder in 4 to 8 oz. of water, juice, soda, coffee or tea until completely dissolved.
5. Drink the solution.
6. Treatment for 2 to 4 days may required to produce a bowel movement.
Keep this and all medications out of the reach of children.
Store at 20° - 25° C (68° - 77° F); excursions permitted to 15° - 30°(59° - 86° F). (See USP Controlled Room Temperature)
Lot # and Exp. Date:
Open here for more product information

PATIENT INFORMATION

Polyethylene Glycol 3350 NF (Polyethylene Glycol 3350 Powder for Oral Solution) is a MEDICAL FOOD prescription only laxative which has been prescribed by your healthcare provider to manage constipation. This product should only be used by the person for whom it was prescribed.
How to take
The dose is 17 grams taken by mouth each day or as directed by your healthcare provider. Measure the dose using the product cap (or use one heaping tablespoon of powder), stir and dissolve in a glass (4 to 8 oz.) of water, juice, soda, coffee, or tea. Taking more than the prescribed dose may cause loss of fluid due to severe diarrhea.
How it will work
Polyethylene Glycol 3350 NF(PEG 3350)NF) softens the stool and increases the frequency of bowel movements by retaining water in the stool. Your first bowel movement will usually happen in two to four days, although results may vary for individual patients.
How long should it take
Polyethylene Glycol 3350 NF achieves the best results when used between one and two weeks. You may discontinue therapy after you have had several satisfactory bowel movements or diarrhea. Should unusual cramps, bloating, or diarrhea occur, consult your physician. Polyethylene Glycol 3350 NF is intended for up to a two week course of therapy. You should not use for a longer time unless directed by your physician.
Next Steps
After successfully completing Polyethylene Glycol 3350 NF therapy (usually between one and two weeks,) please discuss with your healthcare provider lifestyle changes which may produce more regular bowel habits such as adequate dietary and fluid intake, and regular exercise.
Who should not take Polyethylene Glycol 3350 NF
PEG 3350 NF should not be used by children and pregnant women unless prescribed by a physician.
Side Effects/Drug Reactions
Occasionally, Polyethylene Glycol 3350 NF may cause nausea, stomach fullness, cramping, diarrhea and /or gas. Do not take if you have symptoms such as nausea, vomiting, abdominal pain or distension, which may be due to bowel obstruction. On a rare occasions hives and skin rashes have been reported which are suggestive of an allergic reaction. If you get an allergic reaction reaction, you should stop using PEG 3350 NF, and call your physician. if you are allergic to polyethylene glycol, do not use this product.

Polyethylene Glycol 3350 NF Polyethylene Glycol 3350 Powder for Oral Solution

A white powder for reconstitution. Polyethylene Glycol 3350 (Polyethylene Glycol 3350 Powder For Oral Solution) is a synthetic polyglycol having an average molecular weight of 3350. The actual molecular weight is not less than 90.0 percent and not greater than 110.0 percent of the normal value. The chemical formula is HO(C2H4O)nH in which n represents the average number of ethylene groups. Below 55° it is a free flowing white powder freely soluble in water. Polyethylene Glycol 3350 NF is an osmotic agent for the treatment of constipation.

CLINICAL PHARMACOLOGY

Pharmacology: Polyethylene Glycol 3350 NF is an osmotic agent which causes water to be retained with the stool. Essentially, complete recovery of Polyethylene Glycol 3350 NF was shown in normal subjects without constipation. Attempts at recovery of Polyethylene Glycol 3350 NF in constipated patients resulted in incomplete and highly variable recovery. In vitro study showed indirectly that Polyethylene Glycol 3350 NF was not fermented into hydrogen or methane by the colonic mircoflora in human feces. Polyethylene Glycol 3355 NF appears to have no effect on the active absorption or secretion of glucose or electrolytes. There is no evidence of tachyphylaxis.

CLINICAL TRIALS

In one study, patients with less than 3 bowel movements per week were randomized to Polyethylene Glycol 3350 NF, 17 grams or placebo for 14 days. An increase in bowel movement frequency was observed for both treatment groups during the first week of treatment. Polyethylene Glycol 3350 NF was statistically superior to placebo during the second week of treatment. In another study, patients with 3 bowel movements or less per week and/or less than 300 grams of stool per week were randomized to 2 dose levels of Polyethylene Glycol 3350 NF or placebo for 10 days each. Success was defined by an increase in both bowel movement frequency and daily stool weight. For both parameters, superiority of the 17 gram dose of Polyethylene Glycol 3350 NF over the placebo was demonstrated.

INDICATIONS AND USAGE

For the treatment of occasional constipation. This product should be used for 2 weeks or less as directed by a physician.

CONTRAINDICATIONS

Polyethylene Glycol 3350 NF is contraindicated in patients with known or suspected bowel obstruction and patients known to be allergic to polyethylene glycol.

WARNINGS

Patients with symptoms suggestive of bowel obstruction (nausea, vomiting, abdominal pain or distention) should be evaluated to rule out this condition before initiating Polyethylene Glycol 3350 NF therapy.

PRECAUTIONS

General: Patients presenting with complaints of constipation should have a thorough medical history and physical examination to detect associated metabolic endocrine and neurogenic conditions and medications. A diagnostic evaluation should include a structural examination of the colon. Patients should be educated about a good defecatory and eating habits (such as high fiber diets) and lifestyle changes (adequate dietary fiber and fluid intake, regular exercise) which may produce regular bowel habits.
Polyethylene Glycol 3350 NF should be administered after being dissolved in approximately 4 to 8 ounces of water, juice, soda, coffee,or tea.
Information for Patients: Polyethylene Glycol 3350 NF softens stool and increases the frequency of bowel movement by retaining water in the stool. It should always be taken by mouth after being dissolved in 4 to 8 ounces of water, juice, soda, coffee or tea. Should unusual cramps, bloating or diarrhea occur, consult your physician.
Two to four days may be required to produce a bowel movement. This product should be used for 2 weeks or less or as directed by your physician. prolonged, frequent or excessive use of Polyethylene Glyycol 3350 NF may result in electrolyte imbalance and dependency on laxatives.
Laboratory Tests: No clinically significant effects on laboratory tests have been demonstrated.
Drug Interaction: No specific drug interactions have been demonstrated.
Carcinogenesis, Mutagenesis, Impairment of Fertility: Long term carcinogenicity studies, genetic toxicity studies or reproductive toxicity studies in animals have not been performed with Polyethylene Glycol 3350 NF.
Pregnancy: Category C. Animal reproductive studies have not been performed with Polyethylene Glycol 3350 NF. It is not known wheter Polyethylene Glycol 3350 NF can cause fetal harm when administered in a pregnant woman, or can affect reproductive capacity. Polyethylene Glycol 3350 NF should only be administered to a pregnant woman if clearly needed.
Pediatric Use: Safety and effectiveness in pediatric patients has not been established.
Geriatric Use: There is no evidence for special consideration when Polyethylene Glycol 3350 NF is administered to elderly patients. In geriatric nursing home patients a higher incidence of diarrhea occurred at the recommended 17 g dose. If diarrhea occurs Polyethylene Glycol 3350 NF should be discontinued..

ADVERSE REACTIONS

Nausea, abdominal bloating, cramping and flatulence may occur. High doses may produce diarrhea and excessive stool frequency, particularly in elderly nursing home patients. Patients taking other medications containing polyethylene glycol occasionally developed hives suggestive of an allergic reaction.

OVERDOSE

There have been no reports of accidental overdose. In the event of overdose, diarrhea would be the expected major event. If an overdose occurred without conomitant ingestion of fluids, dehydration due to diarrhea may result. Treatment should be terminated and free water administered. The oral LD50 is >50g/kg in mice, rats and rabbits.

DOSAGE AND ADMINISTRATION

The usual dose is 17 grams (about 1 heaping tablespoon) of powder in 4 to 8 ounces of water, juice, soda, coffee or tea daily or as directed by physician. Each bottle of Polyethylene Glycol 3350 NF has a cap that holds 17 grams of laxative powder when filled to the top.Two to four days (48 to 96 hours0 may be required to produce a bowel movement.

HOW SUPPLIED

PEG 3350 NF is supplied in powder form for oral administration after dissolution in water, juice, soda, coffee, or tea.
Rx only.

Keep this and all medication out of the reach of children.

STORAGE

Store at 20°-25°C (68°-77°F): excursions permitted to 15°-30°C (59°-86°F).
(See USP Controlled Room Temperature)

Product Label Product Insert

M.E. Pharmaceuticals, Inc.

58607-700-57
Prescription Powder for Oral Solution
Polyethylene
Gylcol 3350 NF
PEGyLAX
Rx Only
527 Grams
MADE WITH PRIDE IN THE U.S.A.
M.E. Pharmaceuticals, Inc.
Richmond, IN 47374